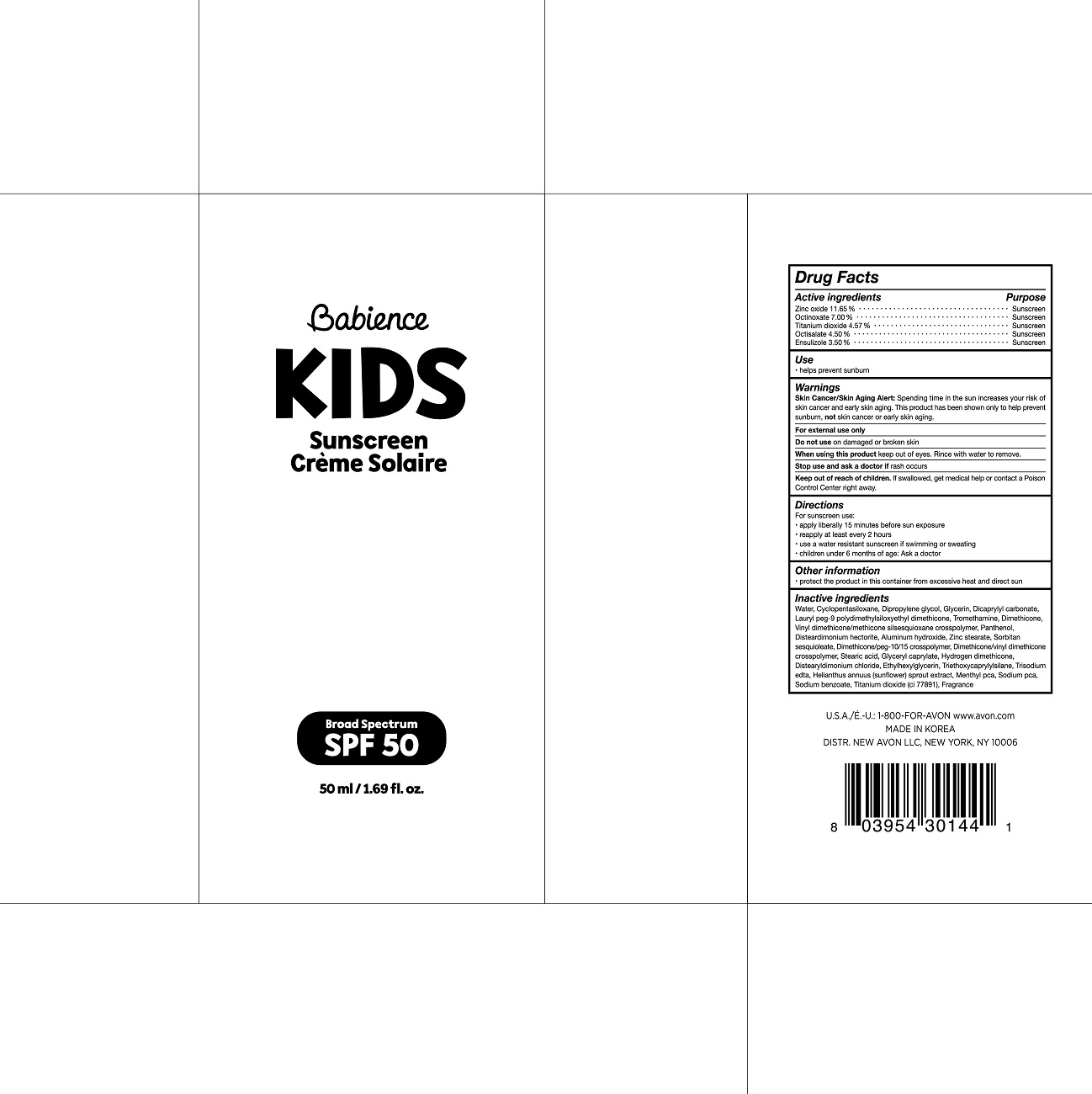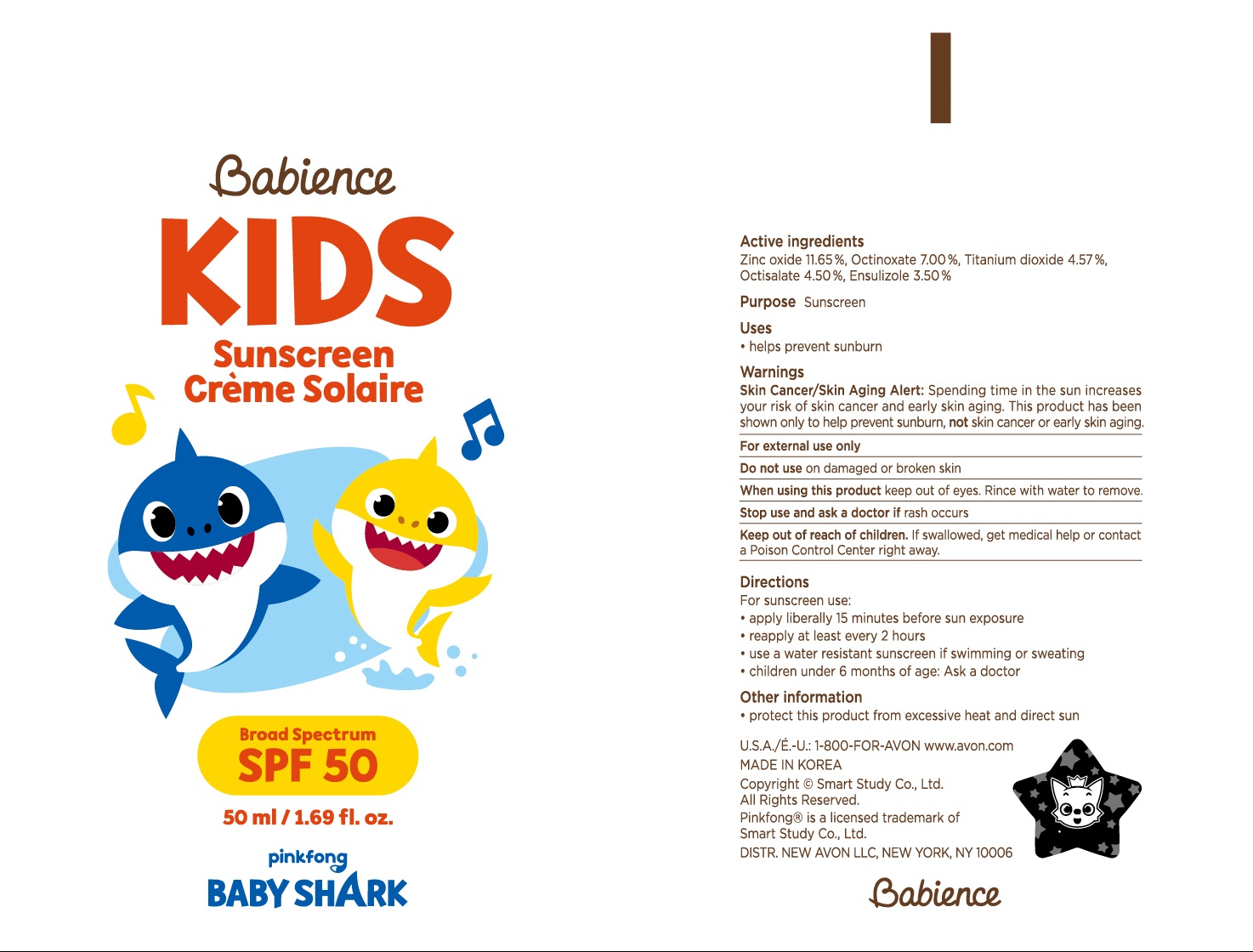 DRUG LABEL: Babience KIDS Sunscreen pinkfong BABY SHARK SPF 50
NDC: 53208-800 | Form: LOTION
Manufacturer: LG H&H Co., Ltd.
Category: otc | Type: HUMAN OTC DRUG LABEL
Date: 20250101

ACTIVE INGREDIENTS: TITANIUM DIOXIDE 2.285 g/50 mL; ENSULIZOLE 1.75 g/50 mL; OCTINOXATE 3.5 g/50 mL; ZINC OXIDE 5.825 g/50 mL; OCTISALATE 2.25 g/50 mL
INACTIVE INGREDIENTS: DICAPRYLYL CARBONATE; LAURYL PEG-9 POLYDIMETHYLSILOXYETHYL DIMETHICONE; DIMETHICONE; VINYL DIMETHICONE/METHICONE SILSESQUIOXANE CROSSPOLYMER; MENTHYL DL-PYRROLIDONECARBOXYLATE; TRIETHOXYCAPRYLYLSILANE; SODIUM BENZOATE; WATER; DIMETHICONE CROSSPOLYMER (450000 MPA.S AT 12% IN CYCLOPENTASILOXANE); DIMETHICONE/VINYL DIMETHICONE CROSSPOLYMER (HARD PARTICLE); ZINC STEARATE; SORBITAN SESQUIOLEATE; ALUMINUM HYDROXIDE; DISTEARYLDIMONIUM CHLORIDE; DIPROPYLENE GLYCOL; TROMETHAMINE; STEARIC ACID; HYDROGEN DIMETHICONE (13 CST); EDETATE TRISODIUM; SODIUM PYRROLIDONE CARBOXYLATE; GLYCERIN; PANTHENOL; GLYCERYL CAPRYLATE; HELIANTHUS ANNUUS SPROUT; ETHYLHEXYLGLYCERIN

53208-800-01 Babience KIDS Sunscreen SPF 50 pinkfong BABY SHARK 50ml

Active ingredients

Ensulizole 3.5%

Octinoxate 7.00%

Octisalate 4.5%

Titanium Dioxide 4.57%

Zinc Oxide 11.65%

Purpose

Sunscreen

USES

- Helps prevent sunburn
- If used as directed with other sun protection measures (see Directions), decreases the risk of skin cancer and early skin aging caused by the sun

Warnings

Skin Cancer/Skin Aging Alert: Spending time in the sun increases your risk of skin cancer and early skin aging. This product has been shown only to help prevent sunburn, notskin cancer or early skin aging.

For external use only

Do not useon damaged or broken skin

WHEN USING

When using this productkeep out of eyes. Rinse with water to remove

Stop use and ask doctorif rash occurs

Keep out of reach of children.If swallowed, get medical help or contact a Poison Control Center right away.

Directions

For sunscreen use:

- apply liberally 15 minutes before sun exposure
- reapply at least every 2 hours
- use a water resistent sunscreen if swimming or sweating
- children under 6 months of age: Ask a doctor

Inactive ingredients

WATER, CYCLOPENTASILOXANE, DIPROPYLENE GLYCOL, GLYCERIN, DICAPRYLYL CARBONATE, LAURYL PEG-9 POLYDIMETHYLSILOXYETHYL DIMETHICONE, TROMETHAMINE, DIMETHICONE, VINYL DIMETHICONE/METHICONE SILSESQUIOXANE CROSSPOLYMER, PANTHENOL, DISTEARDIMONIUM HECTORITE, ALUMINUM HYDROXIDE, ZINC STEARATE, SORBITAN SESQUIOLEATE, DIMETHICONE/PEG-10/15 CROSSPOLYMER, DIMETHICONE/VINYL DIMETHICONE CROSSPOLYMER, STEARIC ACID, GLYCERYL CAPRYLATE, HYDROGEN DIMETHICONE, DISTEARYLDIMONIUM CHLORIDE, ETHYLHEXYLGLYCERIN, TRIETHOXYCAPRYLYLSILANE, TRISODIUM EDTA, HELIANTHUS ANNUS (SUNFLOWER) SRPOUT EXTRACT, MENTHYL PCA, SODIUM PCA, SODIUM BENZOATE, TITANIUM DIOXIDE (CI 77891), FRAGRANCE

Other information

Protect this product in this container from excessive heat and direct sun

U.S.A./E.-U.: 1-800-FOR-AVON www.avon.com

PRINCIPAL DISPLAY PANEL

Babience
KIDS
Sunscreen
Broad Spectrum
SPF 50
50 ml / 1.69 fl. oz.
pinkfong

BABY SHARK

1-800-FOR-AVON www.avon.com

MADE IN KOREA

DIST. NEW AVON LLC, NEW YORK, NY 1006